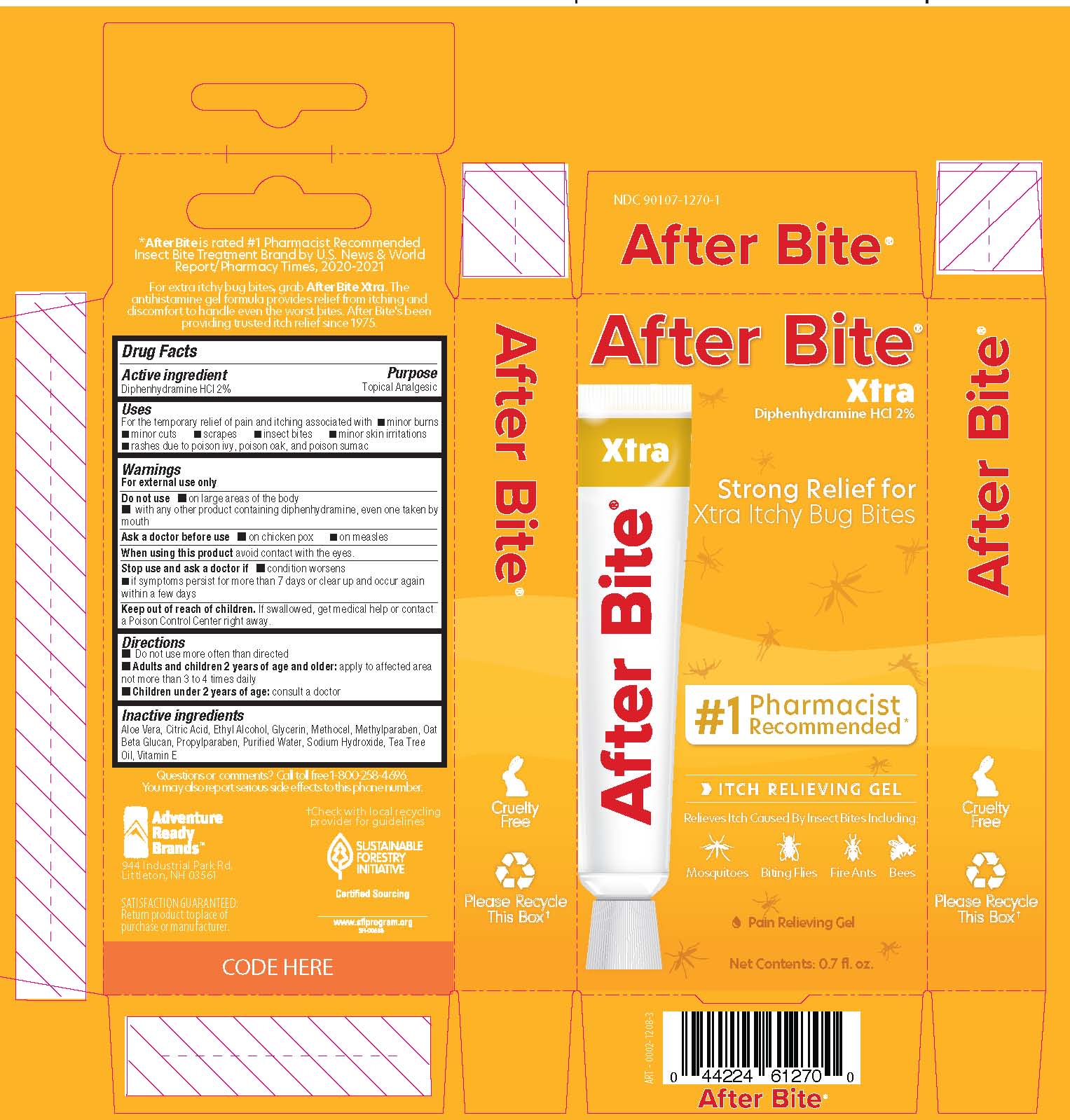 DRUG LABEL: After Bite Xtra
NDC: 90107-1270 | Form: GEL
Manufacturer: Adventure Ready Brands
Category: otc | Type: HUMAN OTC DRUG LABEL
Date: 20241227

ACTIVE INGREDIENTS: DIPHENHYDRAMINE HYDROCHLORIDE 20 mg/1 g
INACTIVE INGREDIENTS: ALOE VERA LEAF; ANHYDROUS CITRIC ACID; ALCOHOL; METHYLPARABEN; TEA TREE OIL; METHYLCELLULOSE (100 CPS); OATMEAL; WATER; SODIUM HYDROXIDE; .ALPHA.-TOCOPHEROL ACETATE; GLYCERIN; PROPYLPARABEN

After Bite Xtra

Active Ingredient

Diphenhydramine HCl 2%

Purpose

Topical Analgesic

Uses

For the temporary relief of pain and itching associated with

- minor burns
- minor cuts
- scrapes
- insect bites
- minor skin irritations
- rashes due to poison ivy, poison oak, and poison sumac

Warnings

For external use only

Do not use

- on large areas of the body
- with any other product containing diphenhydramine, even one taken by mouth

Ask a doctor before use

- on chicken pox
- on measles

When using

When using this product avoid contact with eyes.

Stop use and ask a doctor if

- condition worsens
- if symptoms persist for more than 7 days or clear up and occur again within a few days

Keep out of reach of children. If swallowed, get medical help or contact a Poison Control Center right away.

Directions

- do not use more than directed
- adults and children over 2 years of age and older: apply to affected area not more than 3 to 4 times daily
- children under 2 years of age: ask a doctor

Inactive Ingredients

Aloe Vera, Citric Acid, Ethyl Alcohol, Glycerin, Methocel, Methylparaben, Oat Beta Glucan, Propylparaben, Purified Water, Sodium Hydroxide, Tea Tree Oil, Vitamin E